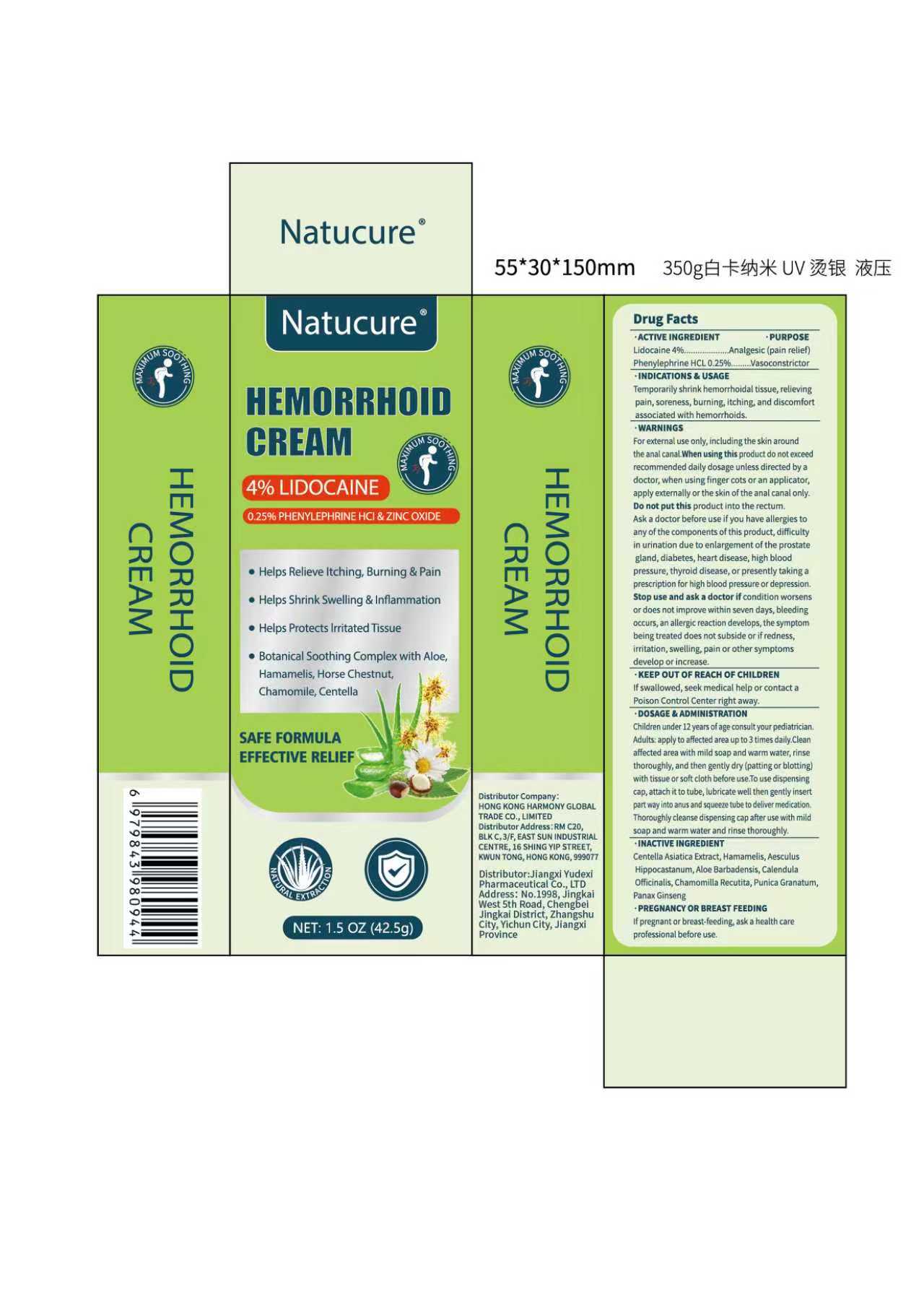 DRUG LABEL: Natucure HEMORRHOID
NDC: 85248-044 | Form: CREAM
Manufacturer: Jiangxi Yudexi Pharmaceutical Co., LTD
Category: otc | Type: HUMAN OTC DRUG LABEL
Date: 20260202

ACTIVE INGREDIENTS: LIDOCAINE 4 g/100 g; PHENYLEPHRINE HYDROCHLORIDE 0.25 g/100 g
INACTIVE INGREDIENTS: MATRICARIA RECUTITA; HAMAMELIS VIRGINIANA LEAF; PUNICA GRANATUM WHOLE; CENTELLA ASIATICA TRITERPENOIDS; PANAX GINSENG FLOWER; HORSE CHESTNUT; ALOE BARBADENSIS LEAF; CALENDULA OFFICINALIS FLOWERING TOP

85248-044

Active Ingredient

Lidocaine 4% Phenylephrine HCL 0.25%

Purpose

Analgesic (pain relief) Vasoconstrictor

Use

Temporarily shrink hemorrhoidal tissue, relieving pain,soreness, burning, itching, and discomfort associated with hemorrhoids.

Warnings

For external use only, including the skin around the anal canal.

Do not use

Do not put this product into the rectum.

When Using

When using this product do not exceed recommended daily dosage unless directed by a doctor, when using finger cots or an applicator, apply externally or the skin of the anal canal only.

Stop Use

Ask a doctor before use if you have allergies to any of the components of this product, difficulty in urination due to enlargement of the prostate gland, diabetes, heart disease, high blood pressure, thyroid disease, or presently taking a prescription for high blood pressure or depression.

Ask Doctor

Stop use and ask a doctor if condition worsens or does not improve
within seven days, bleeding occurs, an allergic reaction develops, the
symptom being treated does not subside or if redness, irritation, swelling, pain or other symptoms develop or increase.

Keep Oot Of Reach Of Children

If swallowed, seek medical help or contact a Poison Control Center right away.

Directions

Children under 12 years of age consult your pediatrician. Adults: apply to affected area up to 3 times daily.Clean affected area with mild soap and warm water, rinse thoroughly, and then gently dry (patting or blotting) with tissue or soft cloth before use.
To use dispensing cap, attach it to tube, lubricate well then gently insert part way into anus and squeeze tube to deliver medication. Thoroughly cleanse dispensing cap after use with mild soap and warm water and rinse thoroughly.

Other information

If pregnant or breast-feeding, ask a health care professional before use.

Inactive ingredients

Centella Asiatica Extract,Hamamelis, AesculusHippocastanum, Aloe Barbadensis, CalendulaOfficinalis, Chamomilla Recutita, Punica Granatum,Panax Ginseng